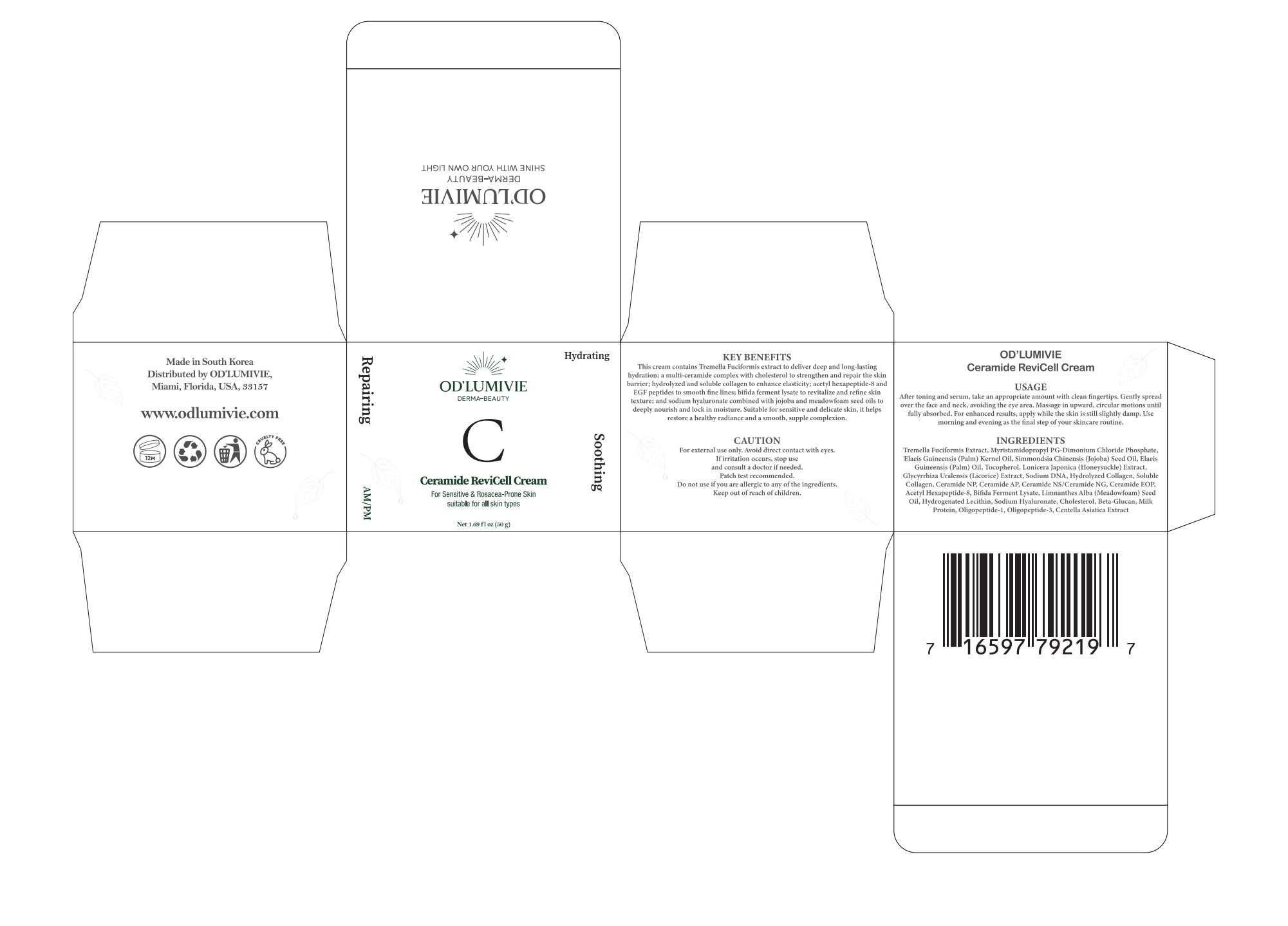 DRUG LABEL: ODLUMIVIE Ceramide ReviCell Cream
NDC: 87036-029 | Form: CREAM
Manufacturer: OD’LUMIVIE
Category: otc | Type: HUMAN OTC DRUG LABEL
Date: 20251111

ACTIVE INGREDIENTS: CERAMIDE NP 1 g/100 g
INACTIVE INGREDIENTS: GLYCYRRHIZA URALENSIS WHOLE; LONICERA JAPONICA WHOLE; MARINE COLLAGEN, SOLUBLE; CERAMIDE AP; SIMMONDSIA CHINENSIS (JOJOBA) SEED OIL; CERAMIDE NS; ELAEIS GUINEENSIS (PALM) OIL; TOCOPHEROL; ACETYL HEXAPEPTIDE-8; CERAMIDE NG; MYRISTAMIDOPROPYL PG-DIMONIUM CHLORIDE PHOSPHATE; TREMELLA FUCIFORMIS WHOLE; ELAEIS GUINEENSIS (PALM) KERNEL OIL; CENTELLA ASIATICA; MILK PROTEIN; CHOLESTEROL; LIMNANTHES ALBA (MEADOWFOAM) SEED OIL; PEG-5 HYDROGENATED LANOLIN; RH-OLIGOPEPTIDE-1; SODIUM HYALURONATE

ACTIVE INGREDIENT

INACTIVE INGREDIENT

INGREDIENTS
Tremella Fuciformis Extract, Myristamidopropyl PG-Dimonium Chloride Phosphate,Elaeis Guineensis (Palm) Kernel Oil, Simmondsia Chinensis (Jojoba) Seed Oil, ElaeisGuineensis (Palm)Oil, Tocopherol, Lonicera Japonica (Honeysuckle) Extract,Glycyrrhiza Uralensis (Licorice) Extract, Sodium DNA, Hydrolyzed Collagen, SolubleCollagen, Ceramide NP, Ceramide AP, Ceramide NS/Ceramide NG, Ceramide EOPAcetyl Hexapeptide-8, Bifda Ferment Lysate, Limnanthes Alba (Meadowfoam) SeedOil, Hydrogenated Lecithin, Sodium Hyaluronate, Cholesterol, Beta-Glucan, MilkProtein, Oligopeptide-1, Oligopeptide-3, Centella Asiatica Extract

PURPOSE

KEY BENEFITS
This cream contains Tremella Fuciformis extract to deliver deep and long-lastinghydration; a multi-ceramide complex with cholesterol to strengthen and repair the skinbarrier; hydrolyzed and soluble collagen to enhance elasticity; acetyl hexapeptide-8 andEGF peptides to smooth fine lines, bifda ferment lysate to revitalize and refine skintexture; and sodium hyaluronate combined with jojoba and meadowfoam seed oils todeeply nourish and lock in moisture. Suitable for sensitive and delicate skin, it helpsrestore a healthy radiance and a smooth, supple complexion.

WARNINGS

CAUTION
For external use only. Avoid direct contact with eyes.If irritation occurs, stop useand consult a doctor ifneeded.Patch test recommended.Do not use if you are allergic to any of the ingredients.Keep out of reach of children.

DO NOT USE

CAUTION
For external use only. Avoid direct contact with eyes.If irritation occurs, stop useand consult a doctor ifneeded.Patch test recommended.Do not use if you are allergic to any of the ingredients.Keep out of reach of children.

KEEP OUT OF REACH OF CHILDREN

CAUTION
For external use only, Avoid direct contact with eyes. Ifirritation occurs, stop useand consult a doctor if needed. Patch test recommended, Do not use if you areallergic to any of the ingredients. Keep out of reach of children.

STOP USE

CAUTION
For external use only, Avoid direct contact with eyes. Ifirritation occurs, stop useand consult a doctor if needed. Patch test recommended, Do not use if you areallergic to any of the ingredients. Keep out of reach of children.

USAGE
After toning and serum, take an appropriate amount with clean fngertips. Gently spreadover the face and neck, avoiding the eye area. Massage in upward, circular motions untilfully absorbed. For enhanced results, apply while the skin is still slightly damp. Usemorning and evening as the fnal step of your skincare routine.

WHEN USING

USAGE
After toning and serum, take an appropriate amount with clean fngertips. Gently spreadover the face and neck, avoiding the eye area. Massage in upward, circular motions untilfully absorbed. For enhanced results, apply while the skin is still slightly damp. Usemorning and evening as the fnal step of your skincare routine.

DOSAGE AND ADMINISTRATION

USAGE
After toning and serum, take an appropriate amount with clean fngertips. Gently spreadover the face and neck, avoiding the eye area. Massage in upward, circular motions untilfully absorbed. For enhanced results, apply while the skin is still slightly damp. Usemorning and evening as the fnal step of your skincare routine.

PACKAGE LABEL

KEY BENEFITS
lhis cream contains lremella Fuciformis extract to deliver deep andlong-lastinghydration; a multi-ceramide complex with cholesterol to strengthen and repair the skinbarrier; hydrolyzed and soluble collagen to enhance elasticity; acetyl hexapeptide-8 andEGF peptides to smooth fne lines; bifida ferment lysate to revitalize and refine skintexture; and sodium hyaluronate combined with jojoba and meadowfoam seed oils todeeply nourish and lock in moisture. Suitable for sensitive and delicate skin, it helps
restore a healthy radiance and a smooth, supple complexion.
CAUTIONFor external use only. Avoid direct contact with eyes.Ifirritation occurs, stop useand consult a doctor ifneeded.Patch test recommended.Do not use if you are allergic to any ofthe ingredients.Keep out of reach of children.
OD'LUMIVIECeramide ReviCell Cream
USAGEAfter toning and serum, take an appropriate amount with clean fingertips. Gently spreadover the face and neck, avoiding the eye area. Massage in upward, circular motions untilfully absorbed, For enhanced results, apply while the skin is still slightly damp. Usemorning and evening as the fnal step ofyour skincare routine.
INGRRDTRN
Tremella Fuciformis Extract, Myristamidopropyl PG-Dimonium Chloride PhosphateElaeis Guineensis (Palm) Kernel Oil, Simmondsia Chinensis (loioba) Seed Oil, ElaeisGuineensis(Palm)Oi,locopherol.loniceraanonica(onevsucke)Extract.Glycyrrhiza Uralensis (Licorice)Extract,Sodium DNA, Hydrolyzed Collagen, SolublCollagen, Ceramide NP, Ceramide AP, Ceramide NS/Ceramide NG, Ceramide EOP,Acetyl Hexapeptide-8, Bifda Ferment Lysate, Limnanthes Alba (Meadowfoam) SeedOil, Hydrogenated Lecithin, Sodium Hyaluronate, Cholesterol, Beta-Glucan, MilkProtein, Oligopeptide-l, Oligopeptide-3, Centella Asiatica Extract